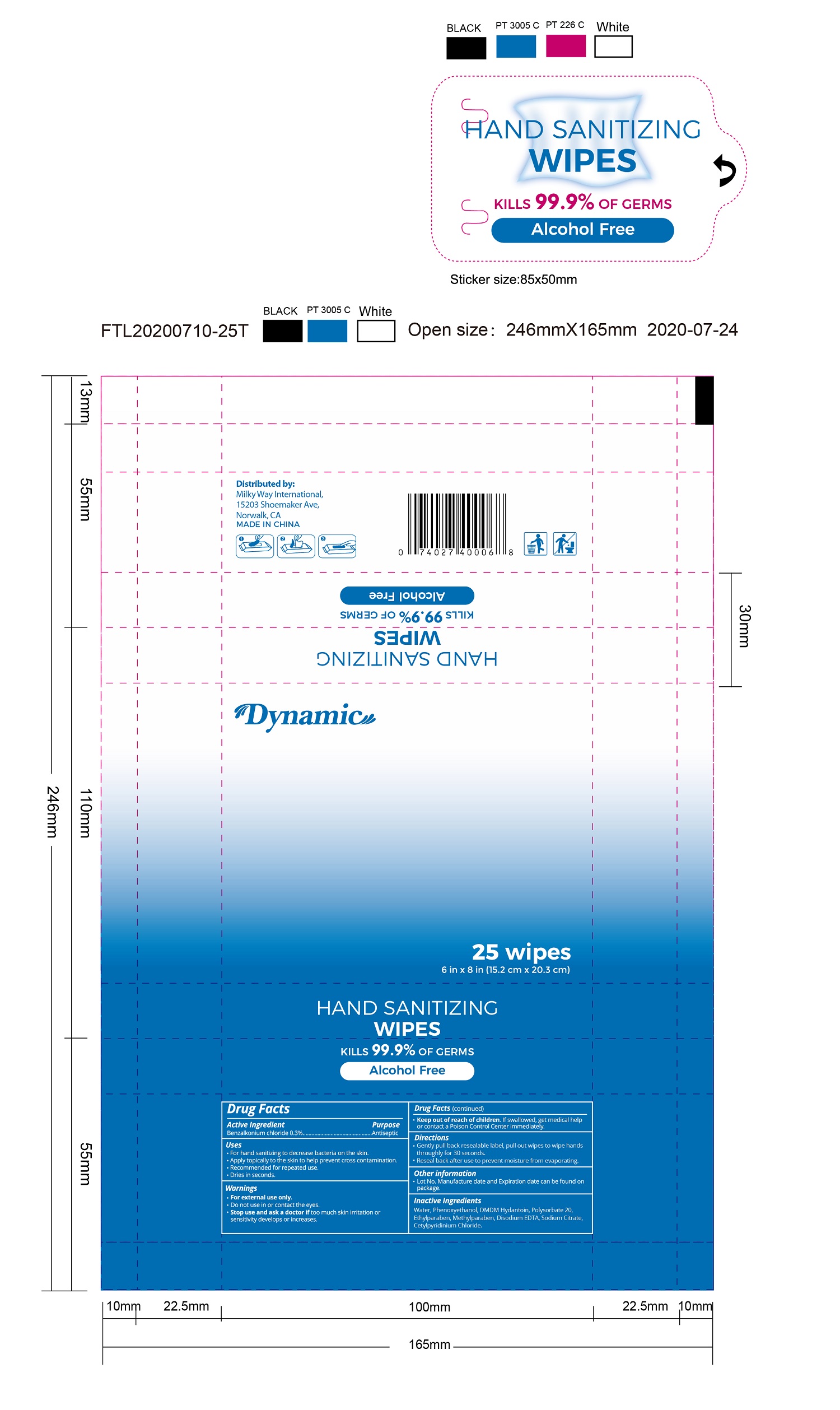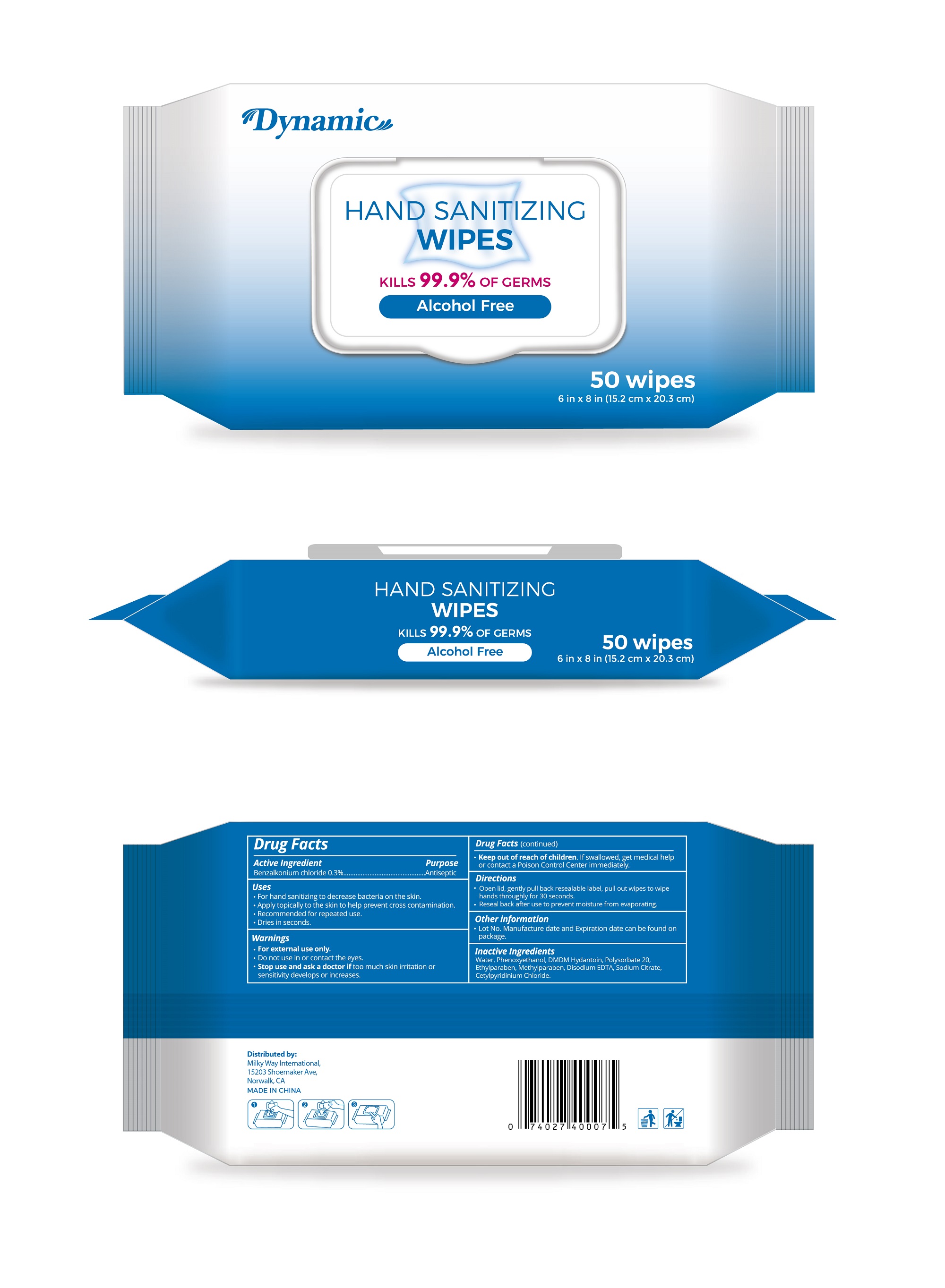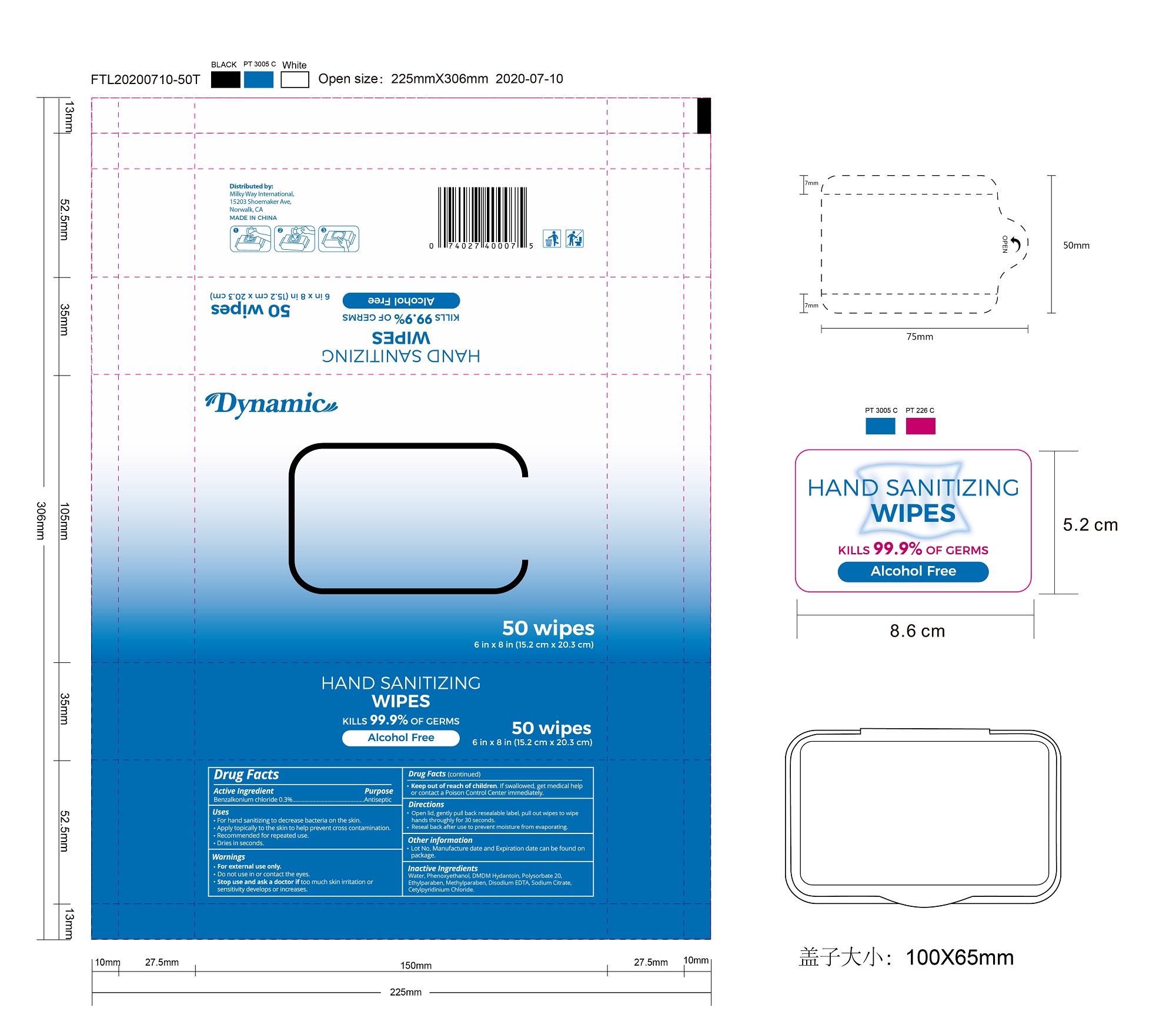 DRUG LABEL: Dynamic Hand Sanitizing Wipes
NDC: 79203-001 | Form: CLOTH
Manufacturer: Milky Way International Trading Corp
Category: otc | Type: HUMAN OTC DRUG LABEL
Date: 20220208

ACTIVE INGREDIENTS: BENZALKONIUM CHLORIDE 0.3 g/100 g
INACTIVE INGREDIENTS: WATER; DISODIUM EDTA-COPPER; POLYSORBATE 20; PHENOXYETHANOL; SODIUM CITRATE; CETYLPYRIDINIUM CHLORIDE; ETHYLPARABEN; DMDM HYDANTOIN; METHYLPARABEN

79203-001 Dynamic hand sanitizing wipes 0.3% Benzalkonium Chloride

Active Ingredient

Purpose

Antiseptic

USE

●For hand sanitizing to decrease bacteria on the skin.
●Apply topically to the skin to help prevent cross contamination.
● Recommended for repeated use.
●Dries in seconds.

Warning

For external use only.
Do not use in or contact the eyes.
Stop use and ask a doctor if too much skin irritation or
sensitivity develops or increases.

keep out of reach of children. If swallowed, contact medical help or call Poison Control immediately.

Directions

Open lid, gently pull back resealable label, pull out wipes to wipe
hands throughly for 30 seconds.
Reseal back after use to prevent moisture from evaporating.

Inactive ingredients

Water, Phenoxyethanol, DMDM Hydantoin, Polysorbate 20,
Ethylparaben, Methylparaben, Disodium EDTA, Sodium Citrate,
Cetylpyridinium Chloride.